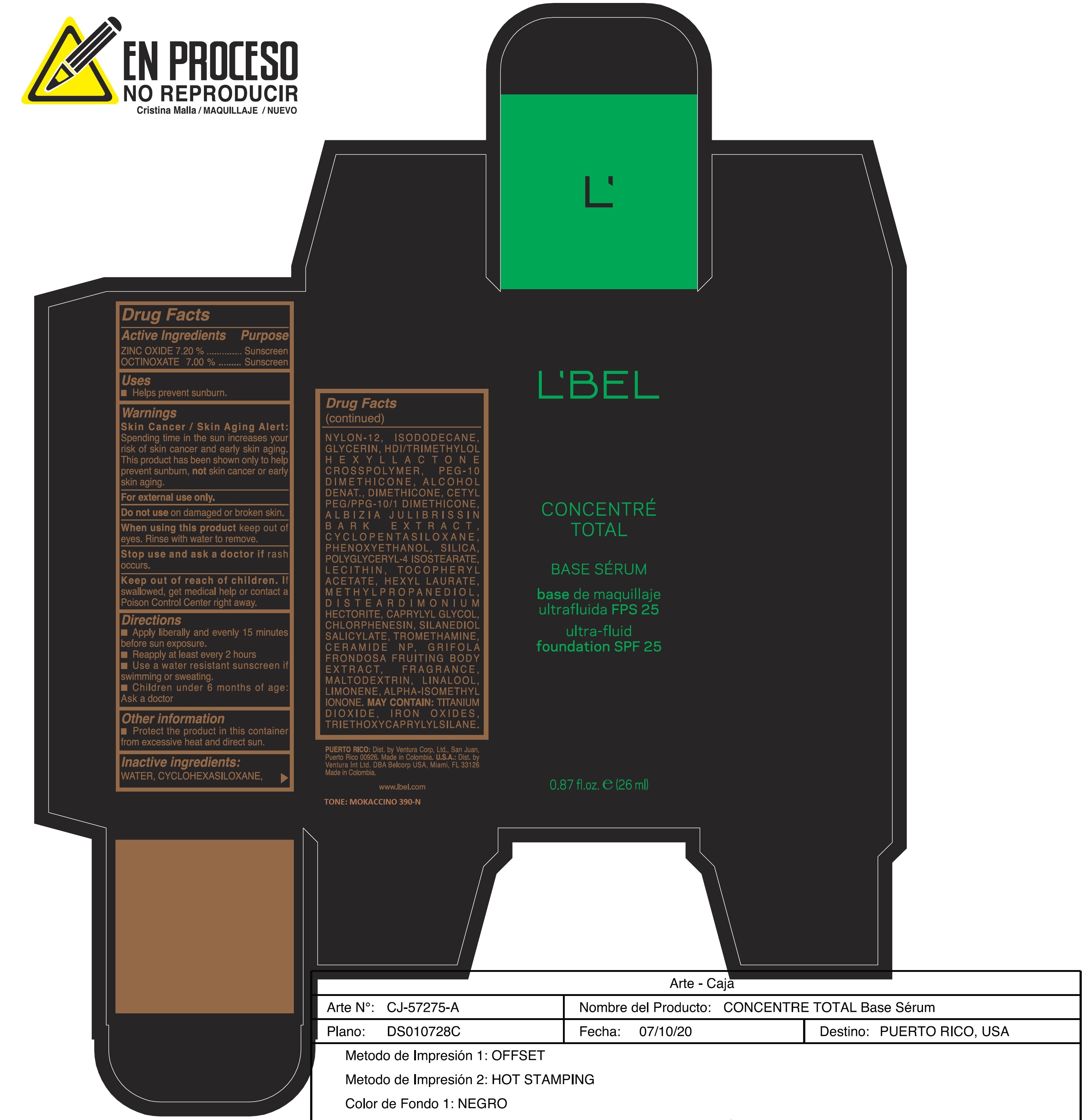 DRUG LABEL: CONCENTRE TOTAL BASE SERUM BASE DE MAQUILLAJE ULTRA-FLUID FOUNDATION SPF 25 MOKACCINO 390-N
NDC: 14783-286 | Form: EMULSION
Manufacturer: Ventura International LTD
Category: otc | Type: HUMAN OTC DRUG LABEL
Date: 20210421

ACTIVE INGREDIENTS: OCTINOXATE 7 g/100 mL; ZINC OXIDE 7.2 g/100 mL
INACTIVE INGREDIENTS: CERAMIDE NP; FERRIC OXIDE YELLOW; HEXAMETHYLENE DIISOCYANATE/TRIMETHYLOL HEXYLLACTONE CROSSPOLYMER; .ALPHA.-TOCOPHEROL ACETATE; MAITAKE; ISODODECANE; POLYGLYCERYL-4 ISOSTEARATE; CAPRYLYL GLYCOL; GLYCERIN; MALTODEXTRIN; ISOMETHYL-.ALPHA.-IONONE; CHLORPHENESIN; TITANIUM DIOXIDE; PHENOXYETHANOL; LINALOOL, (+/-)-; METHYLPROPANEDIOL; FERROSOFERRIC OXIDE; NYLON-12; CETYL PEG/PPG-10/1 DIMETHICONE (HLB 2); HEXYL LAURATE; TROMETHAMINE; DISTEARDIMONIUM HECTORITE; LIMONENE, (+)-; FERRIC OXIDE RED; TRIETHOXYCAPRYLYLSILANE; ALCOHOL; LECITHIN, SUNFLOWER; SILICON DIOXIDE; SILANEDIOL SALICYLATE; DIMETHICONE; PEG-10 DIMETHICONE (600 CST); WATER; CYCLOMETHICONE 6

CONCENTRÉ TOTAL BASE SÉRUM BASE DE MAQUILLAJE ULTRA-FLUID FOUNDATION SPF 25 MOKACCINO 390-N

Active Ingredients Purpose
ZINC OXIDE 7.20 % Sunscreen
OCTINOXATE 7.00 % Sunscreen

Uses
Helps prevent sunburn.

Keep out of reach of children. If swallowed, get medical help or contact a Poison Control Center right away.

Stop use and ask a doctor if rash occurs.

Warnings
Skin Cancer / Skin Aging Alert: Spending time in the sun increases your risk of skin cancer and early skin aging. This product has been shown only to help prevent sunburn, not skin cancer or early skin aging.
For external use only.
Do not use on damaged or broken skin.

When using this product keep out of eyes. Rinse with water to remove.

Directions
Apply liberally and evenly 15 minutes before sun exposure.
Reapply at least every 2 hours
Use a water resistant sunscreen if swimming or sweating.
Children under 6 months of age: Ask a doctor

Other information
Protect the product in this container from excessive heat and direct sun.

Inactive Ingredients:

Water, Cyclohexasiloxane, Nylon-12, Isododecane, Glycerin, HDI/Trimethylol Hexyllactone Crosspolymer, PEG-10 Dimethicone Alcohol Denat., Dimethicone, Cetyl PEG/PPG-10/1 Dimethicone, Albizia Julibrissin Bark Extract, Cyclopentasiloxane, Phenoxyethanol, Silica, Polyglyceryl-4 Isostearate, Lectithin, Tocopheryl Acetate, Hexyl Laurate, Methylpropanediol, Disteardimonium Hectorite, Caprylyl Glycol, Chlorphenesin, Silanediol Salicylate, Tromethamine, Ceramide NP, Grifola Frondosa Fruiting Body Extract, Fragrance, Maltodextrin, Linalool, Limonene, Alpha-Isomethyl Ionone. May Contain: Titanium Dioxide, Iron Oxides, Triethoxycaprylylsilane

390-N

L'BEL

Concentre Total

Base Serum

base de maquillaje ultrafluida FPS 25

ultra-fluid foundation SPF 25

0.87 fl. oz. (26ml)